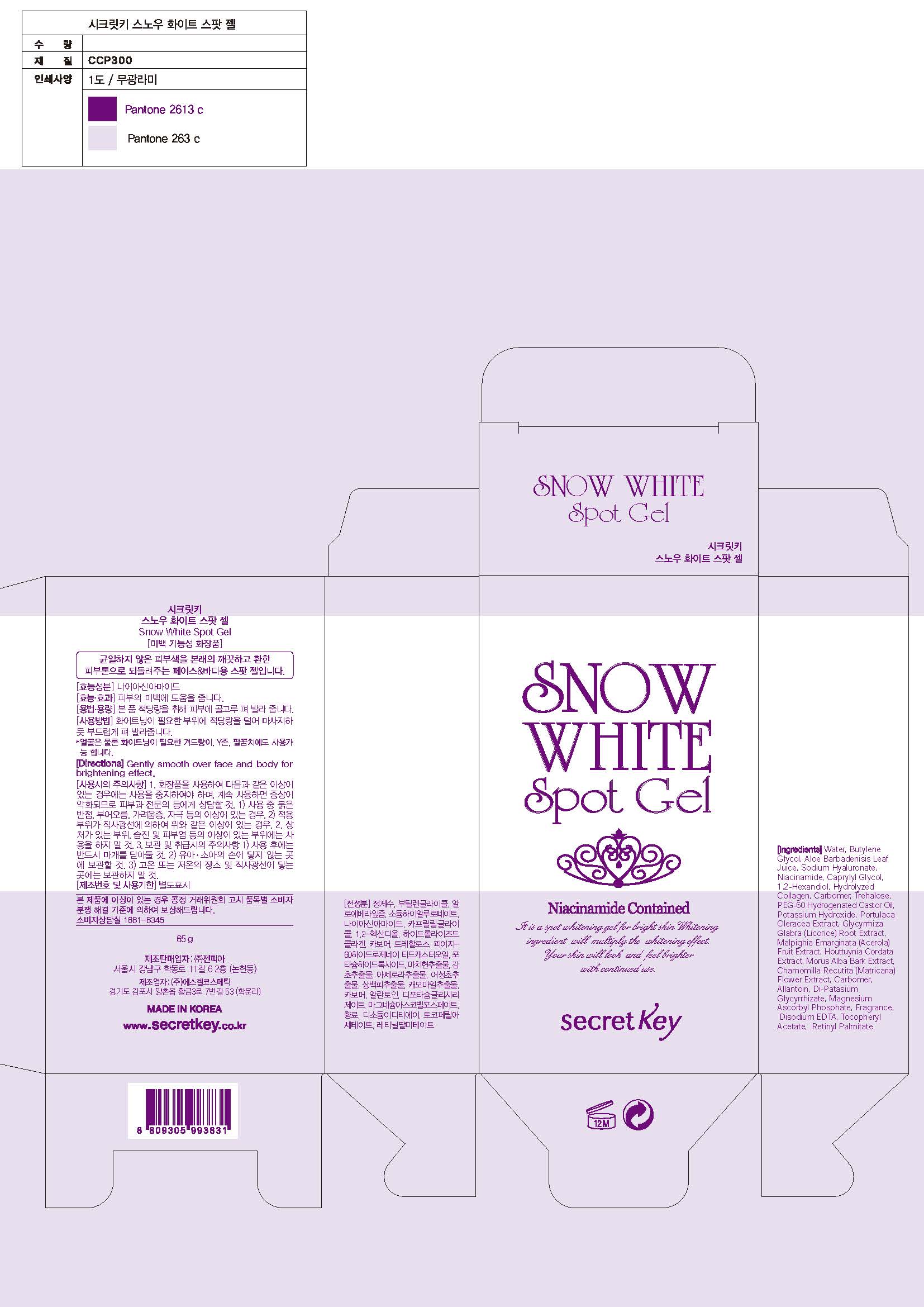 DRUG LABEL: SNOW WHITE SPOT
NDC: 70825-0009 | Form: GEL
Manufacturer: Zenpia
Category: otc | Type: HUMAN OTC DRUG LABEL
Date: 20181219

ACTIVE INGREDIENTS: NIACINAMIDE 2 g/100 g
INACTIVE INGREDIENTS: WATER; BUTYLENE GLYCOL

Drug Facts

ACTIVE INGREDIENT

niacinamide

INACTIVE INGREDIENT

Water, Butylene Glycol, Aloe Barbadensis Leaf Juice, Sodium Hyaluronate, Caprylyl Glycol, 1,2-Hexandiol, Hydrolyzed Collagen, Carbomer, Trehalose, PEG-60 Hydrogenated Castor Oil, Potassium Hydroxide, Portulaca Oleracea Extract, Glycyrrhiza Glabra (Licorice) Root Extract, Malpighia Emarginata (Acerola) Fruit Extract, Houttuynia Cordata Extract, Morus Alba Bark Extract, Chamomilla Recutita (Matricaria) Flower Extract, Allantoin, Dipotassium Glycyrrhizate, Magnesium Ascorbyl Phosphate, Fragrance, Disodium EDTA, Tocopheryl Acetate, Retinyl Palmitate

PURPOSE

skin whitening

keep out or reach of the children

INDICATIONS AND USAGE

Take an appropriate amount and spread on to your skin and tap it.

WARNINGS

1. Do not use in the following cases(Eczema and scalp wounds)
2.Side Effects
1)Due to the use of this druf if rash, irritation, itching and symptopms of hypersnesitivity occur dicontinue use and consult your phamacisr or doctor
3.General Precautions
1)If in contact with the eyes, wash out thoroughty with water If the symptoms are servere, seek medical advice immediately
2)This product is for exeternal use only. Do not use for internal use
4.Storage and handling precautions
1)If possible, avoid direct sunlight and store in cool and area of low humidity
2)In order to maintain the quality of the product and avoid misuse
3)Avoid placing the product near fire and store out in reach of children

DOSAGE AND ADMINISTRATION

for external use only